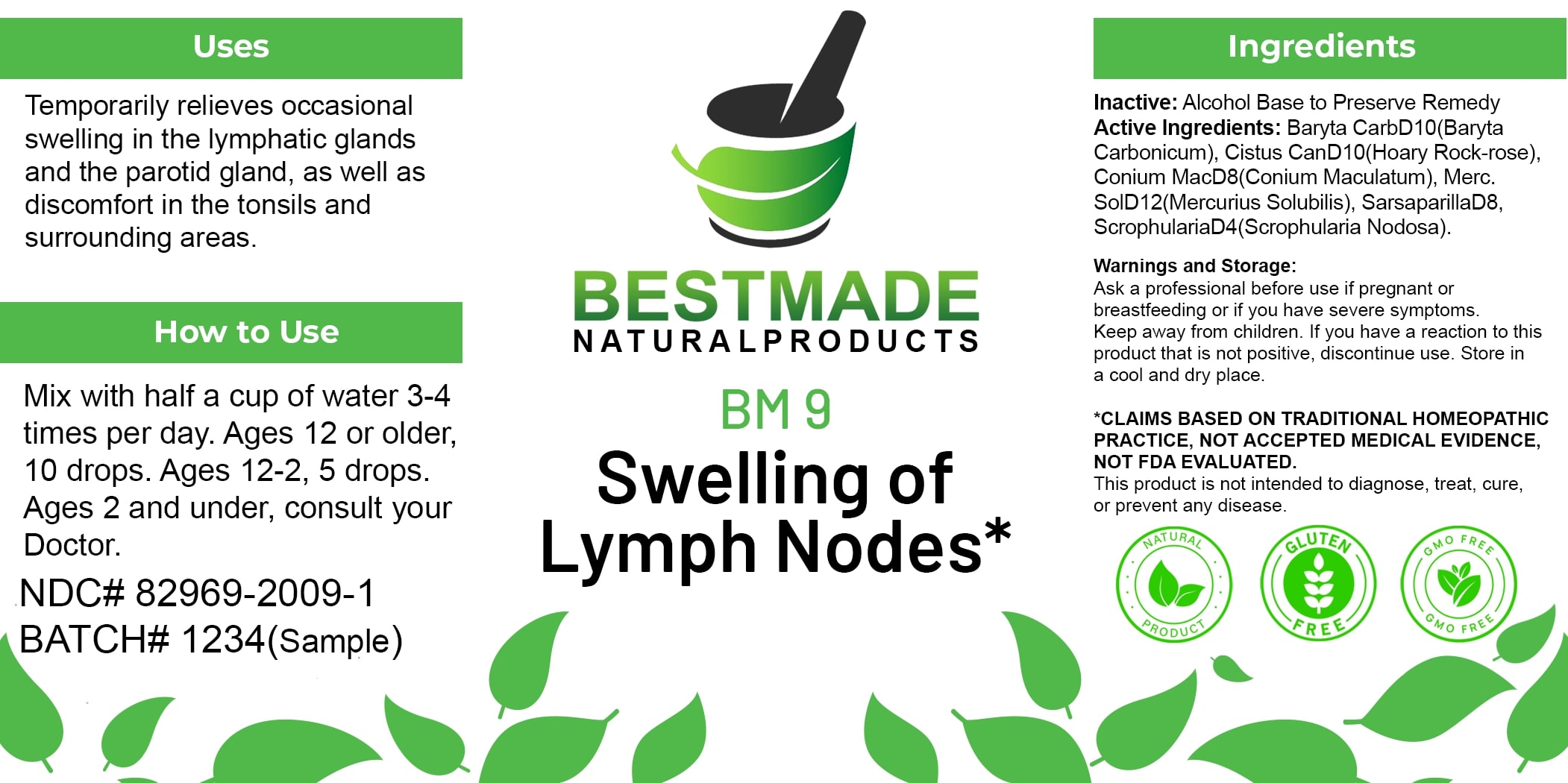 DRUG LABEL: Bestmade Natural Products BM9
NDC: 82969-2009 | Form: LIQUID
Manufacturer: Bestmade Natural Products
Category: homeopathic | Type: HUMAN OTC DRUG LABEL
Date: 20250122

ACTIVE INGREDIENTS: ATROPA BELLADONNA 30 [hp_C]/30 [hp_C]; CONIUM MACULATUM FLOWERING TOP 30 [hp_C]/30 [hp_C]; MERCURIUS SOLUBILIS 30 [hp_C]/30 [hp_C]; HELIANTHEMUM CANADENSE 30 [hp_C]/30 [hp_C]; SCROPHULARIA NODOSA 30 [hp_C]/30 [hp_C]; SMILAX ORNATA ROOT 30 [hp_C]/30 [hp_C]; BARIUM CARBONATE 30 [hp_C]/30 [hp_C]
INACTIVE INGREDIENTS: ALCOHOL 30 [hp_C]/30 [hp_C]

BM9

DOSAGE AND ADMINISTRATION

How to Use

Mix with half a cup of water 3-4 times per day. Ages 12 or older: 10 drops. Ages 12-2: 5 drops. Ages 2 and under: consult your Doctor.

INACTIVE INGREDIENT

Ingredients

Inactive: Alcohol Base to Preserve Remedy

Uses

Temporarily relieves occasional swelling in the lymphatic glands and the parotid gland, as well as discomfort in the tonsils and surrounding areas.

*CLAIMS BASED ON TRADITIONAL HOMEOPATHIC PRACTICE, NOT ACCEPTED MEDICAL EVIDENCE, NOT FDA EVALUATED.
This product is not intended to diagnose, treat, cure, or prevent any disease.

Active Ingredients:

Baryta CarbD10 (Baryta Carbonicum)
Cistus CanD10 (Hoary Rock-rose)
Conium MacD8 (Conium Maculatum)
Merc. SolD12 (Mercurius Solubilis)
SarsaparillaD8
ScrophulariaD4 (Scrophularia Nodosa)

KEEP OUT OF REACH OF CHILDREN

Warnings and Storage

Ask a professional before use if pregnant or breastfeeding or if you have severe symptoms. Keep away from children. If you have a reaction to this product that is not positive, discontinue use. Store in a cool and dry place.

Uses

Temporarily relieves occasional swelling in the lymphatic glands and the parotid gland, as well as discomfort in the tonsils and surrounding areas.

*CLAIMS BASED ON TRADITIONAL HOMEOPATHIC PRACTICE, NOT ACCEPTED MEDICAL EVIDENCE, NOT FDA EVALUATED.
This product is not intended to diagnose, treat, cure, or prevent any disease.

Warnings and Storage

Ask a professional before use if pregnant or breastfeeding or if you have severe symptoms. Keep away from children. If you have a reaction to this product that is not positive, discontinue use. Store in a cool and dry place.

*CLAIMS BASED ON TRADITIONAL HOMEOPATHIC PRACTICE, NOT ACCEPTED MEDICAL EVIDENCE, NOT FDA EVALUATED.
This product is not intended to diagnose, treat, cure, or prevent any disease.

Entire package label